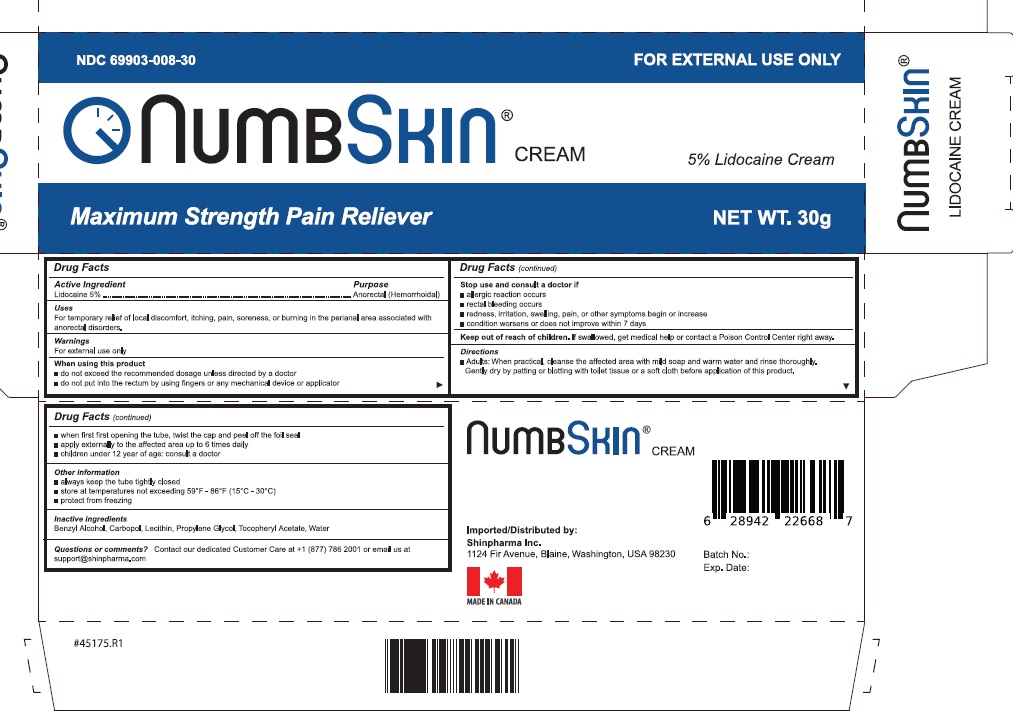 DRUG LABEL: Numbskin Maximum Strength Pain Reliever
NDC: 69903-008 | Form: CREAM
Manufacturer: Shinpharma Inc
Category: otc | Type: HUMAN OTC DRUG LABEL
Date: 20250227

ACTIVE INGREDIENTS: LIDOCAINE 5 g/100 mL
INACTIVE INGREDIENTS: BENZYL ALCOHOL; CARBOMER HOMOPOLYMER, UNSPECIFIED TYPE; LECITHIN, SOYBEAN; PROPYLENE GLYCOL; .ALPHA.-TOCOPHEROL ACETATE; WATER

Numbskin Maximum Strength Pain Reliever

Active ingredient

Lidocaine 5%

Purpose

Anorectal (Hemorrhoidal)

Uses

For temporary relief of local discomfort, itching, soreness or burning in the perianal area associated with anorectal disorders

Warnings

For external use only

When using this product

- do not exceed the recommended daily dosage unless directed by a doctor
- do not put into the rectum by using fingers or any mechanical device or applicator

Stop use and ask a doctor if

- allergic reaction occurs
- rectal bleeding occurs
- redness, irritation, swelling, pain or other symptoms begin or increase
- condition worsens or does not improve within 7 days

KEEP OUT OF REACH OF CHILDREN

If swallowed, get medical help or contact a Poison Control Center right away.

Directions

- Adults: When practical, cleanse the affected area with mild soap and warm water and rinse thoroughly. Gently dry by patting or blotting with toilet tissue or a soft cloth before application of this product.
- When first opening the tube, twist the cap and peel off the foil seal
- Apply externally to the affected area up to 6 times daily
- Children under 12 years: Consult a doctor

Other information

- always keep the tube tighlty closed
- store at temperatures not exceeding 59°F - 86°F (15°C-30°C)
- protect from freezing

Inactive ingredients

Benzyl Alcohol, Carbopol, Letcithin, Propylene Glycol, Tocopheryl Acetate, Water

Questions?

Contact our dedicated Customer Care at +1 (877) 786 2001 or email us at support@shinpharma.com

Principal Display Panel

NDC 69903-007-02

Numbskin Maximum Strength Pain Reliever